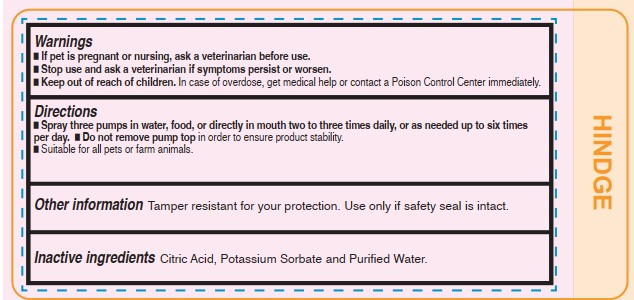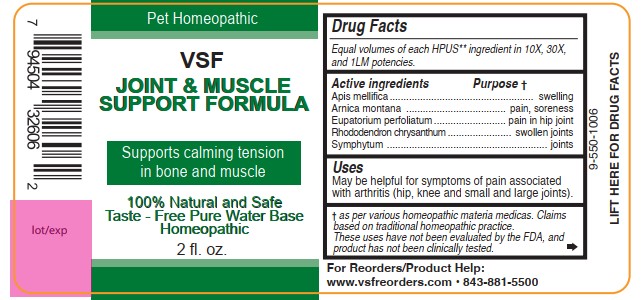 DRUG LABEL: Joint and Muscle Support Formula
NDC: 86100-0016 | Form: LIQUID
Manufacturer: Vsf2 Inc.
Category: homeopathic | Type: OTC ANIMAL DRUG LABEL
Date: 20250909

ACTIVE INGREDIENTS: APIS MELLIFERA 10 [hp_X]/59 mL; ARNICA MONTANA WHOLE 10 [hp_X]/59 mL; EUPATORIUM PERFOLIATUM FLOWERING TOP 10 [hp_X]/59 mL; RHODODENDRON AUREUM LEAF 10 [hp_X]/59 mL; COMFREY ROOT 10 [hp_X]/59 mL
INACTIVE INGREDIENTS: ANHYDROUS CITRIC ACID; POTASSIUM SORBATE; WATER

Joint and Muscle Support Formula

Active ingredients

Drug Facts

Equal volumes of each HPUS** ingredient in 10X, 30X, and 1LM potencies.

Apis mellifica, Arnica montana, Eupatorium perfoliatum, Rhododendron chrysanthum, and Symphytum.

Uses:

May be helpful for symptoms of pain associated with arthritis (hip, knee and small and large joints).

† as per various homeopathic materia medicas. Claims based on traditional homeopathic practice.
These uses have not been evaluated by the FDA, and product has not been clinically tested.

Questions

VSF Joint & Muscle Support Formula 2 fl. oz.

Pet Homeopathic

100% Natural and Safe Taste

Free Pure Water Base

For Reorders/Product Help:

www.vsfreorders.com 843-881-5500

Warnings

- If pet is pregnant or nursing, ask a veterinarian before use.
- Stop use and ask a veterinarian if symptoms persist or worsen.
- Keep out of reach of children. In case of overdose, get medical help or contact a Poison Control Center immediately.

Keep out of reach of children.

In case of overdose, get medical help or contact a Poison Control Center immediately.

Directions

- Spray three pumps in water, food, or directly in mouth two to three times daily, or as needed up to six times per day.
- Do not remove pump top in order to ensure product stability.
- Suitable for all pets or farm animals.

Inactive Ingredients

Citric Acid, Potassium Sorbate, and Purified Water.

Other information

Tamper resistant for your protection.

Use only if safety seal is intact.

Active ingredients Purpose †

Apis mellifica......................................swelling

Arnica montana..................................pain, soreness

Eupatorium perfoliatum.......................pain in hip joints

Rhododendron chrysanthum.................swollen joints

Symphytum........................................joints

† as per various homeopathic materia medicas. Claims based on traditional homeopathic practice.
These uses have not been evaluated by the FDA, and product has not been clinically tested.